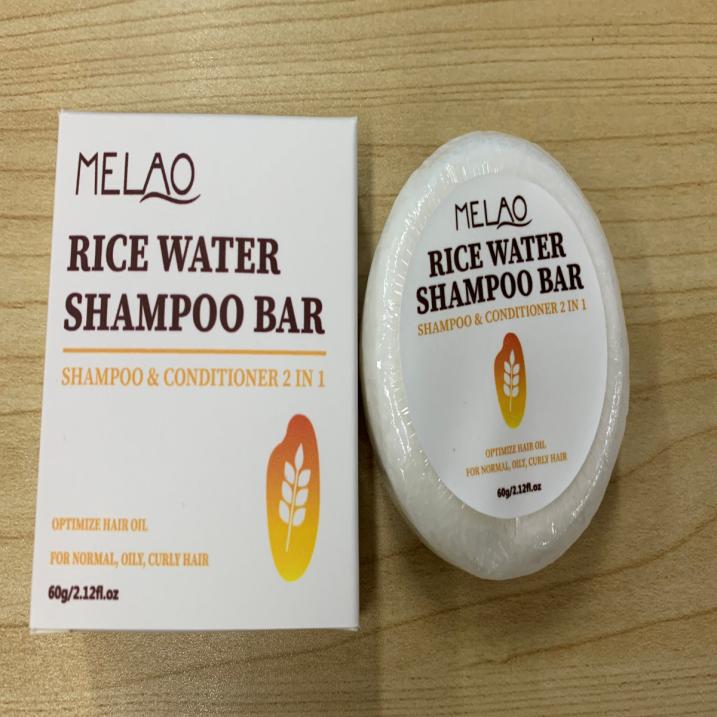 DRUG LABEL: MELAO Rice Sham poo BAR
NDC: 83566-588 | Form: STICK
Manufacturer: Guangzhou Yilong Cosmetics Co., Ltd
Category: otc | Type: HUMAN OTC DRUG LABEL
Date: 20240827

ACTIVE INGREDIENTS: HYDROLYZED RICE PROTEIN (ENZYMATIC; 2000 MW) 3.6 g/100 g
INACTIVE INGREDIENTS: SODIUM COCOYL GLUTAMATE 39 g/100 g; SODIUM LAUROYL GLUTAMATE 9 g/100 g; LIMOSILACTOBACILLUS FERMENTUM ME-3 2.4 g/100 g; .ALPHA.-TOCOPHEROL ACETATE 3.7 g/100 g; PANTHENOL 2.3 g/100 g; COCOS NUCIFERA WHOLE 5 g/100 g; ARGANIA SPINOSA WHOLE 4 g/100 g; OLEA EUROPAEA (OLIVE) OIL UNSAPONIFIABLES 26 g/100 g; ORYZA SATIVA WHOLE 5 g/100 g

MELAO RICE WATER SHAMPOO BAR

Active ingredients

Hydrolyzed Rice Protein 3.60%

Inactive ingredients

Sodium Cocoyl lsethionate 39%

Sodium Lauroyl Glutamate 9%

Olea Europaea (Olive) Fruit Oil 26%

Cocos Nucifera (Coconut) Oil 5%

Oryza Sativa (Rice) Bran Oil 5%

Argania Spinosa Kernel Oil 4%

Tocopherol 3.70%

Lactobacillus/Rice Ferment 2.40%

Panthenol 2.30%

Purpose

Clean and nourish hair

Uses

Step 1: Clean and thoroughly dry your hair.

Step 2: Rotate the bottle cap to open the product.

Step 3: Gently apply to the surface of the hair.

Warning

For external use only.

Stop use and ask a doctor if

rash occurs.

.Do not use

on damaged or broken skin.

When using this product

keep out of eyes. Rinse withwater to remove.

Keep out of reach of children.

-If swallowed, get medical help or contact a Poison Control Center right away

DOSAGE & ADMINISTRATION

Squeeze out an appropriate amount of product and spread evenly on skin